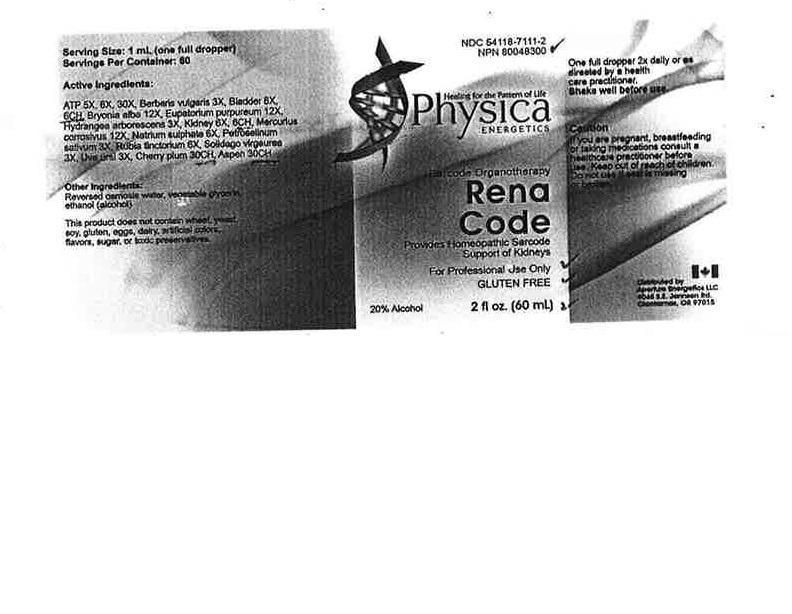 DRUG LABEL: Rena Code
NDC: 54118-7011 | Form: SOLUTION/ DROPS
Manufacturer: ABCO Labratories, Inc.
Category: homeopathic | Type: HUMAN OTC DRUG LABEL
Date: 20150721

ACTIVE INGREDIENTS: ADENOSINE TRIPHOSPHATE 5 [hp_X]/60 mL; BERBERIS VULGARIS WHOLE 3 [hp_X]/60 mL; BOS TAURUS URINARY BLADDER 6 [hp_C]/60 mL; BRYONIA ALBA WHOLE 12 [hp_X]/60 mL; EUPATORIUM PURPUREUM ROOT 12 [hp_X]/60 mL; HYDRANGEA ARBORESCENS WHOLE 12 [hp_X]/60 mL; BEEF KIDNEY 6 [hp_C]/60 mL; MERCURIC CHLORIDE 12 [hp_X]/60 mL; SODIUM SULFATE 6 [hp_X]/60 mL; PARSLEY 3 [hp_X]/60 mL; RUBIA TINCTORUM WHOLE 6 [hp_X]/60 mL; SOLIDAGO VIRGAUREA WHOLE 3 [hp_X]/60 mL; ARCTOSTAPHYLOS UVA-URSI WHOLE 3 [hp_X]/60 mL; CHERRY PLUM 30 [hp_C]/60 mL; POPULUS TREMULA FLOWERING TOP 30 [hp_C]/60 mL
INACTIVE INGREDIENTS: WATER; ALCOHOL; GLYCERIN

Rena Code

WARNINGS

- If you are pregnant, breastfeeding or taking medications consult a healthcare practitioner before use.
- Keep out of reach of children.
- Do not use if seal is missing or broken.

KEEP OUT OF REACH OF CHILDREN!

INDICATIONS AND USAGE

Porvides Homeopathic Sarcode Support of Kidneys

PURPOSE

Sarcode Organotherapy

INACTIVE INGREDIENT

Reversed osmosis water, vegetable glycerin, ethanol (alcohol).

ACTIVE INGREDIENT

ATP 5x, 8x, 30x, Berberis Vulgaris 3x, Bladder 6x, 6c, Bryonia Alba 12x, Eupatorium Purpureum 12x, Hydrangea Arborescens 3x, Kidney 6x, 6c, Mercuius Corrosivus 12x, Natrium Sulphate 6x, Petroselinum Sativum 3x, Rubia Tinctorium 6x, Solidago Virgaurea 3x, Uva Ursi 3x, Cherry Plum 30c, Aspen Flowers 30c.

DOSAGE AND ADMINISTRATION

- One full dropper 2x daily or as directed by a healthcare practitioner.
- Shake well before use.